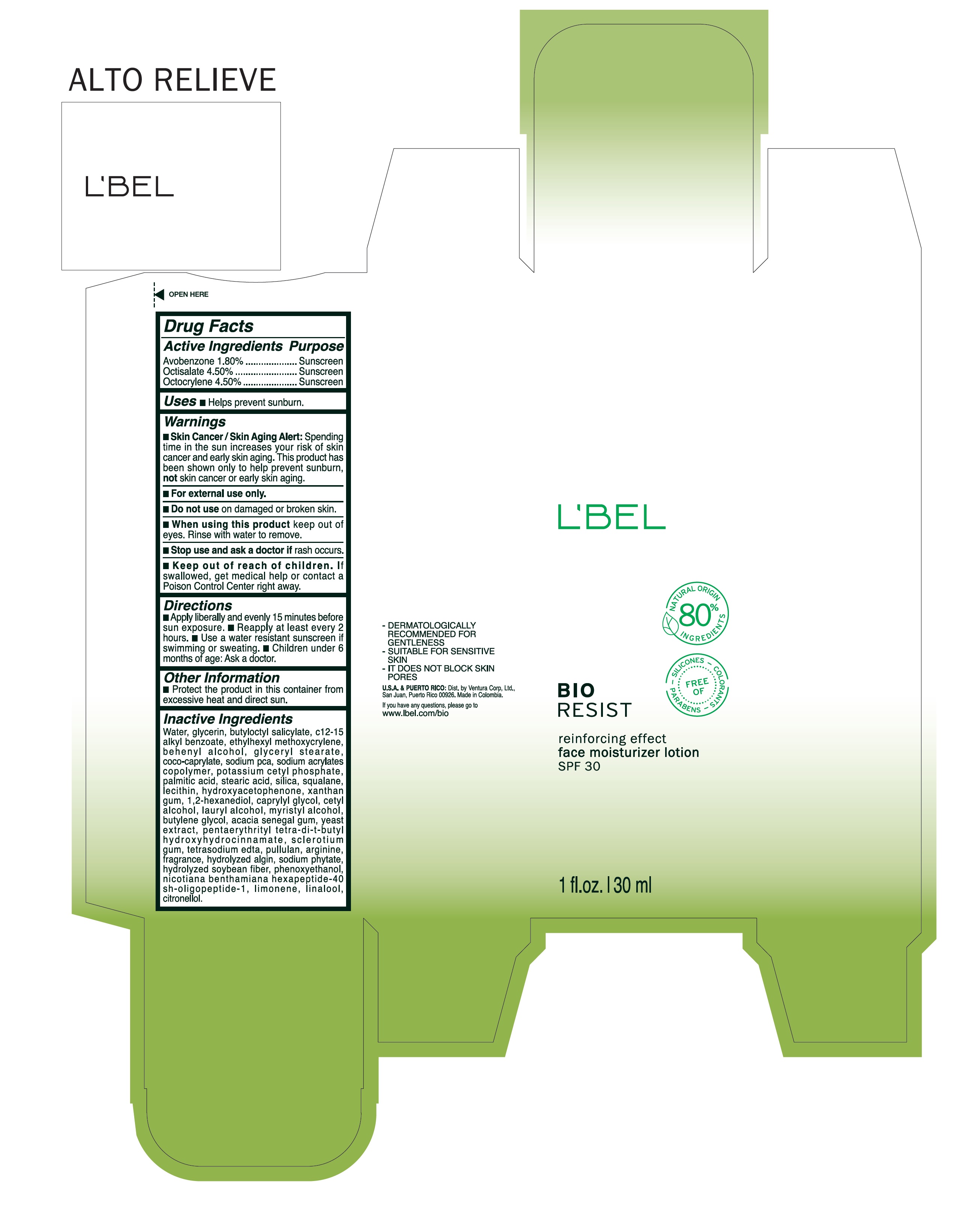 DRUG LABEL: Bioresist reinforcing effect face moisturizer SPF 30
NDC: 14141-142 | Form: CREAM
Manufacturer: BEL STAR S A
Category: otc | Type: HUMAN OTC DRUG LABEL
Date: 20250619

ACTIVE INGREDIENTS: OCTISALATE 4.5 g/100 mL; OCTOCRYLENE 4.5 g/100 mL; AVOBENZONE 1.8 g/100 mL
INACTIVE INGREDIENTS: MYRISTYL ALCOHOL; ACACIA; YEAST, UNSPECIFIED; LIMONENE, (+)-; LINALOOL, (+/-)-; .BETA.-CITRONELLOL, (R)-; STEARIC ACID; SILICON DIOXIDE; LECITHIN, SOYBEAN; CAPRYLYL GLYCOL; BUTYLOCTYL SALICYLATE; DOCOSANOL; GLYCERYL MONOSTEARATE; COCO-CAPRYLATE; WATER; ALKYL (C12-15) BENZOATE; ETHYLHEXYL METHOXYCRYLENE; ARGININE; SODIUM PYRROLIDONE CARBOXYLATE; POTASSIUM CETYL PHOSPHATE; PALMITIC ACID; BETASIZOFIRAN; EDETATE SODIUM; GLYCERIN; PENTAERYTHRITOL TETRAKIS(3-(3,5-DI-TERT-BUTYL-4-HYDROXYPHENYL)PROPIONATE); PULLULAN; PHYTATE SODIUM; PHENOXYETHANOL; LAURYL ALCOHOL; BUTYLENE GLYCOL; SQUALANE; HYDROXYACETOPHENONE; XANTHAN GUM; 1,2-HEXANEDIOL; CETYL ALCOHOL; GELATIN HYDROLYSATE (PORCINE SKIN, MW 3000)

Bioresist reinforcing effect face moisturizer Lotion SPF 30

Active Ingredients Purpose

Avobenzone 1.80% Sunscreen

Octisalate 4.50% Sunscreen

Octocrylene 4.50% Sunscreen

Uses

Helps prevent Sunburn

Keep out of reach of children. If swallowed, get medical help or contact a Poison Control Center right away

Stop use and ask a doctor if rash occurs

WARNINGS

Skin Cancer/Skin Aging Alert: Spending time in the sun increases your risk of skin cancer and early skin aging. This product has been shown only to help prevent sunburn, not skin cancer or early skin aging.

For external use only

Do not use on damaged or broken skin .

When using this product keep out of eyes. Rinse with water to remove.

Directions

- Apply liberally and evenly 15 minutes before sun exposure
- reapply at least every 2 hours
- use a water resistant sunscreen if swimming or sweating
- children under 6 months of age: ask a doctor

Other Information

- Protect the product in this container from excessive heat and direct sun.

Inactive ingredients

Water, glycerin, butyloctyl salicylate, c12-15 alkyl benzoate, ethylhexyl methoxycrylene, behenyl alcohol, glyceryl stearate, coco-caprylate, sodium pca, sodium acrylates copolymer, potassium cetyl phosphate, palmitic acid, stearic acid, silica, squalane, lecithin, hydroxyacetophenone, xanthan gum, 1,2- hexandiol, caprylyl glycol, cetyl alcohol, lauryl alcohol, myristyl alcohol, butylene glycol, acacia senegal gum, yeast extract, pentaerythrityl tetra-di-t-butyl hydroxyhydrocinnamate, sclerotium gum, tetrasodium edta, pullulan, arginine, fragrance, hydrolyzed algin, sodium phytate, hydrolyzed soybean fiber, phenoxyethanol, nicotiana benthamiana hexapeptide-40 sh-oligopeptide-1, limonene, linalool, citronellol.